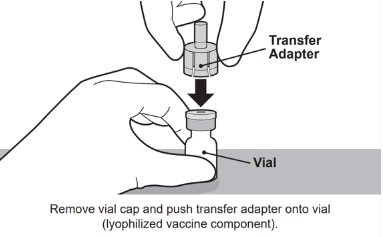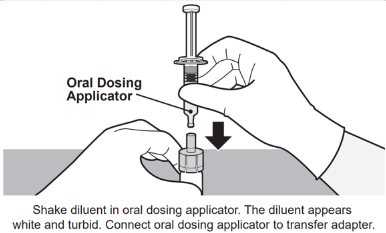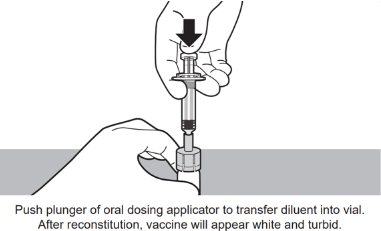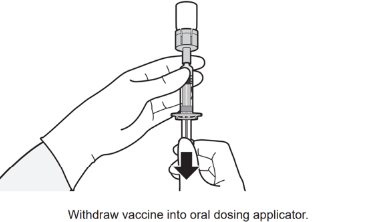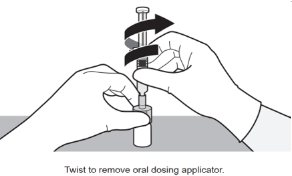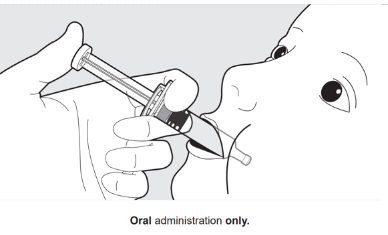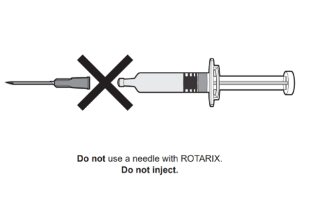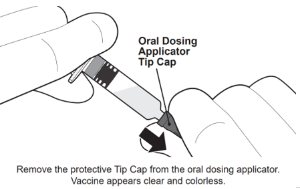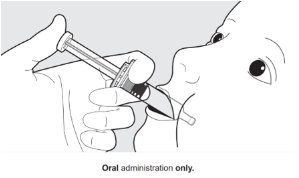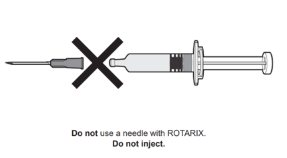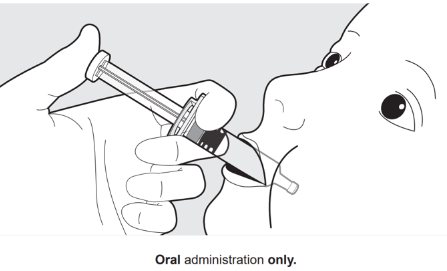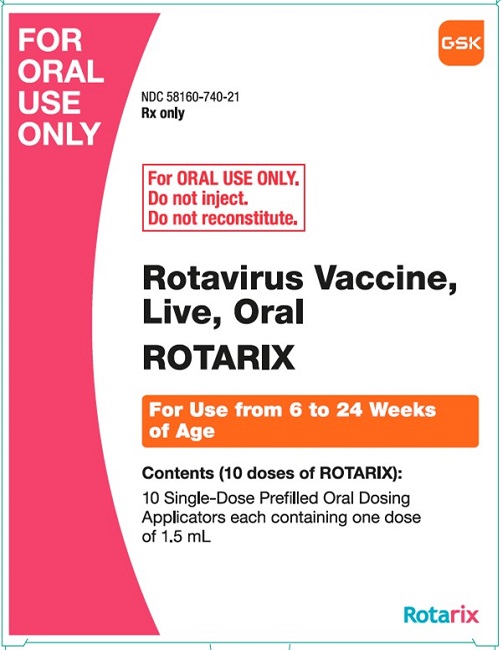 DRUG LABEL: Rotarix
NDC: 58160-740 | Form: SOLUTION
Manufacturer: GlaxoSmithKline Biologicals SA
Category: other | Type: VACCINE LABEL
Date: 20240124

ACTIVE INGREDIENTS: HUMAN ROTAVIRUS A TYPE G1P(8) STRAIN RIX4414 LIVE ANTIGEN 1000 [CCID_50]/1 mL
INACTIVE INGREDIENTS: SODIUM ADIPATE; SODIUM CHLORIDE; POTASSIUM CHLORIDE; MAGNESIUM SULFATE, UNSPECIFIED FORM; FERRIC NITRATE; SODIUM PHOSPHATE, MONOBASIC, UNSPECIFIED FORM; SODIUM PYRUVATE; ANHYDROUS DEXTROSE; CYSTINE; TYROSINE; GLUTAMINE; CALCIUM CHLORIDE; SODIUM BICARBONATE; SUCROSE; WATER

HIGHLIGHTS OF PRESCRIBING INFORMATION

These highlights do not include all the information needed to use ROTARIX safely and effectively. See full prescribing information for ROTARIX.
ROTARIX (Rotavirus Vaccine, Live, Oral)
Suspension, for oral use
Initial U.S. Approval: 2008

1 INDICATIONS AND USAGE

ROTARIX is a vaccine indicated for the prevention of rotavirus gastroenteritis caused by G1 and non-G1 types (G3, G4, and G9). ROTARIX is approved for use in infants 6 weeks and up to 24 weeks of age. (1)

2 DOSAGE AND ADMINISTRATION

FOR ORAL USE ONLY.

ROTARIX is supplied as either:

- Vial and oral dosing applicator presentation: The vial contains the lyophilized vaccine component and the oral dosing applicator contains the diluent. The contents of the vial must be reconstituted with the diluent to form ROTARIX prior to administration (2.1), or
- Oral dosing applicator only presentation: The oral dosing applicator contains ROTARIX and does NOT require reconstitution or dilution before use. (2.1)

Schedule

- Administer first dose to infants beginning at 6 weeks of age. (2.3)
- Administer second dose after an interval of at least 4 weeks and up to 24 weeks of age. (2.3)

3 DOSAGE FORMS AND STRENGTHS

Suspension for oral use.

- Vial and oral dosing applicator presentation: a single dose is 1 mL. (3)
- Oral dosing applicator only presentation: a single dose is 1.5 mL. (3)

4 CONTRAINDICATIONS

- A demonstrated history of hypersensitivity to the vaccine or any component of the vaccine. (4.1, 11)
- History of uncorrected congenital malformation of the gastrointestinal tract that would predispose the infant to intussusception. (4.2)
- History of intussusception. (4.3)
- History of Severe Combined Immunodeficiency Disease (SCID). (4.4, 6.2)

5 WARNINGS AND PRECAUTIONS

- The tip caps of the prefilled oral dosing applicators contain natural rubber latex which may cause allergic reactions. (5.1)
- Administration of ROTARIX in infants suffering from acute diarrhea or vomiting should be delayed. Safety and effectiveness of ROTARIX in infants with chronic gastrointestinal disorders have not been evaluated. (5.2)
- Safety and effectiveness of ROTARIX in infants with known primary or secondary immunodeficiencies have not been established. (5.3)
- In a postmarketing study, cases of intussusception were observed in temporal association within 31 days following the first dose of ROTARIX, with a clustering of cases in the first 7 days. (5.5, 6.2)

6 ADVERSE REACTIONS

Common (≥5%) solicited adverse reactions included fussiness/irritability, cough/runny nose, fever, loss of appetite, and vomiting. (6.1)

To report SUSPECTED ADVERSE REACTIONS, contact GlaxoSmithKline at 1-888-825-5249 or VAERS at 1-800-822-7967 or www.vaers.hhs.gov.

FULL PRESCRIBING INFORMATION

1 INDICATIONS AND USAGE

ROTARIX is indicated for the prevention of rotavirus gastroenteritis caused by G1 and non-G1 types (G3, G4, and G9) when administered as a 2-dose series [see Clinical Studies (14.3)]. ROTARIX is approved for use in infants 6 weeks and up to 24 weeks of age.

2 DOSAGE AND ADMINISTRATION

For oral use only.

2.1 ROTARIX Presentations

ROTARIX is supplied in two presentations, a vial and oral dosing applicator presentation and an oral dosing applicator only presentation.

Vial and Oral Dosing Applicator Presentation

The vial contains the lyophilized vaccine component, and the oral dosing applicator contains the diluent. The contents of the vial must be reconstituted with the diluent to form ROTARIX prior to administration.

Oral Dosing Applicator Only Presentation

The oral dosing applicator only presentation contains ROTARIX and does NOT require reconstitution or dilution before use.

2.2 Preparation and Administration

Vial and Oral Dosing Applicator Presentation

Use accompanying diluent to reconstitute the lyophilized vaccine component to form ROTARIX. After reconstitution, each dose of 1 mL is administered orally.

See Figure 1 for preparation and administration steps.

Figure 1. Preparation and Administration Steps of Vial and Oral Dosing Applicator Presentation

For oral administration only. Have the infant seated in a reclining position. Place the oral dosing applicator towards the inner cheek. Administer the entire contents of the oral dosing applicator into the infant’s mouth.

Oral Dosing Applicator Only Presentation

The ROTARIX oral dosing applicator only presentation does NOT require reconstitution or dilution before use. Each dose of 1.5 mL is administered orally.

See Figure 2 for preparation and administration steps.

Figure 2. Preparation and Administration Steps of Oral Dosing Applicator Only Presentation

For oral administration only. Have the infant seated in a reclining position. Place the oral dosing applicator towards the inner cheek. Administer the entire contents of the oral dosing applicator into the infant’s mouth.

2.3 Dosing and Schedule

The vaccination series consists of two doses administered orally. The first dose should be administered to infants beginning at 6 weeks of age. There should be an interval of at least 4 weeks between the first and second dose. The 2-dose series should be completed by 24 weeks of age.

Safety and effectiveness have not been evaluated if ROTARIX were administered for the first dose and another rotavirus vaccine were administered for the second dose or vice versa.

In the event that the infant spits out or regurgitates most of the vaccine dose, a single replacement dose may be considered at the same vaccination visit.

2.4 Infant Feeding

Breastfeeding was permitted in clinical studies. There was no evidence to suggest that breastfeeding reduced the protection against rotavirus gastroenteritis afforded by ROTARIX. There are no restrictions on the infant’s liquid consumption, including breast milk, either before or after vaccination with ROTARIX.

3 DOSAGE FORMS AND STRENGTHS

Suspension for Oral Use

- Vial and oral dosing applicator presentation: after reconstitution a single dose is 1 mL.
- Oral dosing applicator only presentation: a single dose is 1.5 mL.

4 CONTRAINDICATIONS

4.1 Hypersensitivity

A demonstrated history of hypersensitivity to any component of the vaccine.

Infants who develop symptoms suggestive of hypersensitivity after receiving a dose of ROTARIX should not receive further doses of ROTARIX.

4.2 Gastrointestinal Tract Congenital Malformation

Infants with a history of uncorrected congenital malformation of the gastrointestinal tract (such as Meckel’s diverticulum) that would predispose the infant for intussusception should not receive ROTARIX.

4.3 History of Intussusception

Infants with a history of intussusception should not receive ROTARIX [see Warnings and Precautions (5.5)]. In postmarketing experience, intussusception resulting in death following a second dose has been reported following a history of intussusception after the first dose [see Adverse Reactions (6.2)].

4.4 Severe Combined Immunodeficiency Disease

Infants with Severe Combined Immunodeficiency Disease (SCID) should not receive ROTARIX. Postmarketing reports of gastroenteritis, including severe diarrhea and prolonged shedding of vaccine virus, have been reported in infants who were administered live, oral rotavirus vaccines and later identified as having SCID [see Adverse Reactions (6.2)].

5 WARNINGS AND PRECAUTIONS

5.1 Latex

The tip caps of the prefilled oral dosing applicators contain natural rubber latex which may cause allergic reactions.

5.2 Gastrointestinal Disorders

Administration of ROTARIX should be delayed in infants suffering from acute diarrhea or vomiting.

Safety and effectiveness of ROTARIX in infants with chronic gastrointestinal disorders have not been evaluated. [See Contraindications (4.2).]

5.3 Altered Immunocompetence

Safety and effectiveness of ROTARIX in infants with known primary or secondary immunodeficiencies, including infants with human immunodeficiency virus (HIV), infants on immunosuppressive therapy, or infants with malignant neoplasms affecting the bone marrow or lymphatic system have not been established.

5.4 Shedding and Transmission

Rotavirus shedding in stool occurs after vaccination with peak excretion occurring around Day 7 after Dose 1.

One clinical trial demonstrated that vaccinees transmit vaccine virus to healthy seronegative contacts [see Clinical Pharmacology (12.2)].

The potential for transmission of vaccine virus following vaccination should be weighed against the possibility of acquiring and transmitting natural rotavirus. Caution is advised when considering whether to administer ROTARIX to individuals with immunodeficient close contacts, such as individuals with malignancies, primary immunodeficiency or receiving immunosuppressive therapy.

5.5 Intussusception

Following administration of a previously licensed oral live rhesus rotavirus-based vaccine, an increased risk of intussusception was observed.^1 The risk of intussusception with ROTARIX was evaluated in a pre-licensure randomized, placebo-controlled safety study (including 63,225 infants) conducted in Latin America and Finland. No increased risk of intussusception was observed in this clinical trial following administration of ROTARIX when compared with placebo. [See Adverse Reactions (6.1).]

In a postmarketing, observational study conducted in Mexico, cases of intussusception were observed in temporal association within 31 days following the first dose of ROTARIX, with a clustering of cases in the first 7 days. [See Adverse Reactions (6.2).]

Other postmarketing observational studies conducted in Brazil and Australia also suggest an increased risk of intussusception within the first 7 days following the second dose of ROTARIX.^2,3 [See Adverse Reactions (6.2).]

In worldwide passive postmarketing surveillance, cases of intussusception have been reported in temporal association with ROTARIX [see Adverse Reactions (6.2)].

5.6 Post-Exposure Prophylaxis

Safety and effectiveness of ROTARIX when administered after exposure to rotavirus have not been evaluated.

6 ADVERSE REACTIONS

6.1 Clinical Trials Experience

Because clinical trials are conducted under widely varying conditions, adverse reaction rates observed in the clinical trials of a vaccine cannot be directly compared with rates in the clinical trials of another vaccine and may not reflect the rates observed in practice.

There are two formulations of ROTARIX: a reconstituted lyophilized formulation (supplied in a vial and oral dosing applicator presentation) and a liquid formulation (supplied in an oral dosing applicator only presentation) [see Description (11)]. Safety data accrued with each formulation is relevant to the other because each contains the same live, attenuated rotavirus strain and is manufactured using a similar process.

Common (≥5%) solicited adverse reactions included fussiness/irritability, cough/runny nose, fever, loss of appetite, and vomiting.

Solicited adverse reactions, unsolicited adverse events, serious adverse events (SAEs), and cases of intussusception were collected in 7 clinical studies (Studies 1 to 7; NCT00729001, NCT00385320, NCT00429481, NCT00757770, NCT00140686, NCT00169455, NCT00137930). Cases of intussusception and SAEs were collected in an additional large safety study (Study 8; NCT00140673) that compared ROTARIX (reconstituted lyophilized formulation) to placebo. Solicited adverse reactions, unsolicited adverse events, and SAEs were collected in 3 clinical studies (Studies 9 to 11; NCT02914184, NCT03207750, NCT03954743) that compared the two ROTARIX formulations.

Clinical Trials Experience with ROTARIX (Reconstituted Lyophilized Formulation)

Studies 1 to 8 evaluated a total of 71,209 infants who received ROTARIX (n = 36,755) or placebo (n = 34,454). The racial distribution for these studies was as follows: Hispanic 73.4%, White 16.2%, Black 1.0%, and other 9.4%; 51% were male.

Solicited Adverse Reactions: In 7 clinical studies (Studies 1 to 7), detailed safety information was collected by parents/guardians for 8 consecutive days following vaccination with ROTARIX (i.e., day of vaccination and the next 7 days). A diary card was completed to record fussiness/irritability, cough/runny nose, the infant’s temperature, loss of appetite, vomiting, or diarrhea on a daily basis during the first week following each dose of ROTARIX or placebo. Adverse reactions among recipients of ROTARIX and placebo occurred at similar rates (Table 1).

Table 1. Solicited Adverse Reactions within 8 Days following Doses 1 and 2 of ROTARIX or Placebo (Total Vaccinated Cohort)
Adverse Reaction | Dose 1 |  | Dose 2
Adverse Reaction | ROTARIX | Placebo | ROTARIX | Placebo
Adverse Reaction | n = 3,284 | n = 2,013 | n = 3,201 | n = 1,973
Adverse Reaction | % | % | % | %
Fussiness/irritabilitya | 52 | 52 | 42 | 42
Cough/runny noseb | 28 | 30 | 31 | 33
Feverc | 25 | 33 | 28 | 34
Loss of appetited | 25 | 25 | 21 | 21
Vomiting | 13 | 11 | 8 | 8
Diarrhea | 4 | 3 | 3 | 3
Total vaccinated cohort = All vaccinated infants for whom safety data were available.
n = Number of infants for whom at least one symptom sheet was completed.
a Defined as crying more than usual.
b Data not collected in 1 of 7 studies; Dose 1: ROTARIX n = 2,583; placebo n = 1,897; Dose 2: ROTARIX n = 2,522; placebo n = 1,863.
c Defined as temperature ≥100.4°F (≥38.0°C) rectally or ≥99.5°F (≥37.5°C) orally.
d Defined as eating less than usual.

Unsolicited Adverse Reactions: Infants were monitored for unsolicited serious and non-SAEs that occurred in the 31-day period following vaccination in 7 clinical studies (Studies 1 to 7). The following adverse reactions occurred at a statistically higher incidence (95% Confidence Interval [CI] of Relative Risk [RR] excluding 1) among recipients of ROTARIX (n = 5,082) as compared with placebo recipients (n = 2,902): irritability (ROTARIX 11.4%, placebo 8.7%) and flatulence (ROTARIX 2.2%, placebo 1.3%).

Serious Adverse Reactions: Infants were monitored for SAEs that occurred in the 31-day period following vaccination in 8 clinical studies (Studies 1 to 8). Serious adverse reactions occurred in 1.7% of recipients of ROTARIX (n = 36,755) as compared with 1.9% of placebo recipients (n = 34,454). Among placebo recipients, diarrhea (placebo 0.07%, ROTARIX 0.02%), dehydration (placebo 0.06%, ROTARIX 0.02%), and gastroenteritis (placebo 0.3%, ROTARIX 0.2%) occurred at a statistically higher incidence (95% CI of RR excluding 1) as compared with recipients of ROTARIX.

Deaths: During the entire course of 8 clinical studies (Studies 1 to 8), there were 68 (0.19%) deaths following administration of ROTARIX (n = 36,755) and 50 (0.15%) deaths following placebo administration (n = 34,454). The most commonly reported cause of death following vaccination was pneumonia, which was observed in 19 (0.05%) recipients of ROTARIX and 10 (0.03%) placebo recipients (RR: 1.74, 95% CI: 0.76, 4.23).

Intussusception: In a controlled safety study (Study 8) conducted in Latin America and Finland, the risk of intussusception was evaluated in 63,225 infants (31,673 received ROTARIX and 31,552 received placebo). Infants were monitored by active surveillance including independent, complementary methods (prospective hospital surveillance and parent reporting at scheduled study visits) to identify potential cases of intussusception within 31 days after vaccination and, in a subset of 20,169 infants (10,159 received ROTARIX and 10,010 received placebo), up to one year after the first dose.

No increased risk of intussusception following administration of ROTARIX was observed within a 31-day period following any dose, and rates were comparable to the placebo group after a median of 100 days (Table 2). In a subset of 20,169 infants (10,159 received ROTARIX and 10,010 received placebo) followed up to one year after Dose 1, there were 4 cases of intussusception with ROTARIX compared with 14 cases of intussusception with placebo (RR: 0.28 [95% CI: 0.10, 0.81]). All of the infants who developed intussusception recovered without sequelae.

Table 2. Intussusception and Relative Risk with ROTARIX Compared with Placebo
Confirmed Cases of Intussusception | ROTARIX | Placebo
Confirmed Cases of Intussusception | n = 31,673 | n = 31,552
Within 31 days following diagnosis after any dose | 6 | 7
Relative Risk (95% CI) | 0.85 (0.30, 2.42)
Within 100 days following Dose 1a | 9 | 16
Relative Risk (95% CI) | 0.56 (0.25, 1.24)
CI = Confidence Interval.
a Median duration after Dose 1 (follow-up visit at 30 to 90 days after Dose 2).

Among vaccine recipients, there were no confirmed cases of intussusception within the 0- to 14-day period after the first dose (Table 3), which was the period of highest risk for the previously licensed oral live rhesus rotavirus-based vaccine.^1

Table 3. Intussusception Cases by Day Range in Relation to Dose
Day Range | Dose 1 |  | Dose 2 |  | Any Dose
Day Range | ROTARIX | Placebo | ROTARIX | Placebo | ROTARIX | Placebo
Day Range | n = 31,673 | n = 31,552 | n = 29,616 | n = 29,465 | n = 31,673 | n = 31,552
0-7 | 0 | 0 | 2 | 0 | 2 | 0
8-14 | 0 | 0 | 0 | 2 | 0 | 2
15-21 | 1 | 1 | 2 | 1 | 3 | 2
22-30 | 0 | 1 | 1 | 2 | 1 | 3
Total (0-30) | 1 | 2 | 5 | 5 | 6 | 7

Kawasaki Disease − Results from Controlled and Uncontrolled Clinical Studies: Kawasaki disease has been reported in 18 (0.035%) recipients of ROTARIX and 9 (0.021%) placebo recipients from 16 completed or ongoing clinical trials (Studies 1 to 8; Studies 12 to 14, NCT00425737, NCT00346892, NCT00139347; Studies 15 to 17, NCT00197210 for the 3 studies; Studies 18 and 19, NCT00334607, NCT00382772). Of the 27 cases, 5 occurred following ROTARIX in clinical trials that were either not placebo-controlled or 1:1 randomized. In placebo-controlled trials, Kawasaki disease was reported in 17 recipients of ROTARIX and 9 placebo recipients (RR: 1.71 [95% CI: 0.71, 4.38]). Three of the 27 cases were reported within 30 days post-vaccination: 2 cases (ROTARIX = 1, placebo = 1) were from placebo-controlled trials (RR: 1.00 [95% CI: 0.01, 78.35]) and one case following ROTARIX was from a non–placebo-controlled trial. Among recipients of ROTARIX, the time of onset after study dose ranged 3 days to 19 months.

Clinical Trials Comparing the Two ROTARIX Formulations

The safety of the ROTARIX liquid formulation was evaluated in 3 randomized clinical studies (Studies 9 to 11). A total of 4,223 infants received ROTARIX (liquid formulation, n = 2,507; reconstituted lyophilized formulation, n = 1,716). The racial distribution for these 3 studies was as follows: Asian 24.4%, White 63.2%, Black or African American 5.1%, and other 7.3%; 49.7% were male.

In Study 10, a concomitant vaccine administration study conducted in United States, 1,272 infants received ROTARIX (liquid formulation, n = 632; reconstituted lyophilized formulation, n = 640). The racial distribution for this study was as follows: Asian 3.3%, White 73.8%, Black or African American 11.9%, and other 10.9%; 51.5% were male.

In Studies 9 to 11, solicited general adverse reactions (cough/runny nose, diarrhea, fever, irritability/fussiness, loss of appetite and vomiting) were recorded by the parent on diary cards during the 8 days after each vaccination (day of vaccination and 7 following days). Unsolicited adverse events were assessed within 31 days following each vaccination (day of vaccination and 30 following days). SAEs were assessed through 6 months after the last dose.

Solicited Adverse Reactions: In Study 10, solicited adverse reactions among recipients of the two ROTARIX formulations are presented in the Table 4:

Table 4. Solicited Adverse Reactions within 8 Days following Doses 1 and 2 of ROTARIX (Liquid or Reconstituted Lyophilized Formulation), Study 10 Total Vaccinated Cohort
Adverse Reactions | Dose 1 |  |  |  | Dose 2
Adverse Reactions | ROTARIX (Liquid Formulation); n = 632 |  | ROTARIX (Reconstituted Lyophilized Formulation); n = 640 |  | ROTARIX (Liquid Formulation); n = 607 |  | ROTARIX (Reconstituted Lyophilized Formulation); n = 609
Adverse Reactions | Overall% | G3% | Overall% | G3% | Overall% | G3% | Overall% | G3%
Fussiness/irritabilitya | 70.9 | 9.2 | 71.6 | 8.8 | 72.5 | 13.7 | 70.1 | 11.8
Cough/runny noseb | 27.2 | 0.5 | 28.1 | 1.3 | 36.9 | 3.8 | 36.5 | 3.6
Feverc | 5.7 | 0.3 | 5.0 | 0.3 | 10.5 | 0.3 | 12.3 | 0.7
Loss of appetited | 32.3 | 0.2 | 33.4 | 0.9 | 29.5 | 1.2 | 29.2 | 1.8
Vomitinge | 17.4 | 2.8 | 16.4 | 3.4 | 13.7 | 4.0 | 12.8 | 3.3
Diarrheaf | 6.2 | 0.2 | 5.6 | 0.8 | 5.6 | 0.5 | 4.3 | 0.3
G3 = Grade 3.
Total vaccinated cohort = All vaccinated infants for whom safety data were available.
n = Number of infants who received the specified dose.
a Overall: Defined as crying more than usual. Grade 3: Crying that could not be comforted/prevented normal activity.
b Grade 3 cough/runny nose: cough/runny nose that prevented daily activity.
c Overall: Defined as temperature ≥100.4°F (≥38.0°C). Grade 3: Defined as temperature >103.1 F (>39.5°C).
d Overall: Defined as eating less than usual. Grade 3: Defined as not eating at all.
e Overall: Defined as 1 or more episodes of forceful emptying of partially digested stomach contents ≥1 hour after feeding within a day. Grade 3: ≥3 episodes of vomiting/day.
f Overall: Defined as passage of 3 or more looser than normal stools within a day. Grade 3: ≥6 looser than normal stools/day.

Unsolicited Adverse Events: Infants were monitored for unsolicited serious and non-SAEs that occurred in the 31-day period following vaccination in Studies 9 to 11. There were no notable differences in the occurrence and frequency of unsolicited adverse events between the groups.

Serious Adverse Events: During the entire course of Studies 9 to 11, SAEs occurred in 4.7% of recipients of ROTARIX liquid formulation (n = 2,507) as compared with 4.4% of ROTARIX reconstituted lyophilized formulation recipients (n = 1,716).

During the entire course of Studies 9 to 11, there was 1 fatal SAE (with diagnosis of sudden infant death syndrome) following administration of ROTARIX liquid formulation (Study 10). The SAE was assessed as not causally related to the vaccination.

Among participants in Studies 9 to 11, 2 intussusception cases were reported. One subject from Study 10 experienced intussusception 8 days after receiving the second dose of ROTARIX (reconstituted lyophilized formulation). The event was considered possibly related to ROTARIX. One subject from Study 9 experienced intussusception 133 days after receiving the second dose of ROTARIX (liquid formulation); the event was not considered related to ROTARIX. Both subjects were hospitalized, and the outcome of intussusception was reported as resolved.

6.2 Postmarketing Experience

The temporal association between vaccination with ROTARIX and intussusception was evaluated in a hospital-based active surveillance study that identified infants with intussusception at participating hospitals in Mexico. Using a self-controlled case series method,^4 the incidence of intussusception during the first 7 days after receipt of ROTARIX and during the 31-day period after receipt of ROTARIX was compared with a control period. The control period was from birth to one year, excluding the pre-defined risk period (first 7 days or first 31 days post-vaccination, respectively).

Over a 2-year period, the participating hospitals provided health services to approximately 1 million infants under 1 year of age. Among 750 infants with intussusception, the relative incidence of intussusception in the 31‑day period after the first dose of ROTARIX compared with the control period was 1.96 (95.5% CI: 1.46, 2.63)]; the relative incidence of intussusception in the first 7 days after the first dose of ROTARIX compared with the control period was 6.07 (95.5% CI: 4.20, 8.63).

The Mexico study did not take into account all medical conditions that may predispose infants to intussusception. The results may not be generalizable to U.S. infants who have a lower background rate of intussusception than Mexican infants. However, if a temporal increase in the risk for intussusception following ROTARIX similar in magnitude to that observed in the Mexico study does exist in U.S. infants, it is estimated that approximately 1 to 3 additional cases of intussusception hospitalizations would occur per 100,000 vaccinated infants in the U.S. within 7 days following the first dose of ROTARIX. In the first year of life, the background rate of intussusception hospitalizations in the U.S. has been estimated to be approximately 34 per 100,000 infants.^5

Other postmarketing observational studies conducted in Brazil and Australia also suggest an increased risk of intussusception within the first 7 days following the second dose of ROTARIX.^2,3

Worldwide passive postmarketing surveillance data suggest that most cases of intussusception reported following ROTARIX occur in the 7-day period after the first dose.

The following adverse reactions have been identified during postapproval use of ROTARIX. Because these reactions are reported voluntarily from a population of uncertain size, it is not always possible to reliably estimate their frequency or establish a causal relationship to vaccination.

Gastrointestinal Disorders

Intussusception (including death), recurrent intussusception (including death), hematochezia, gastroenteritis with vaccine viral shedding in infants with SCID.

Blood and Lymphatic System Disorders

Idiopathic thrombocytopenic purpura.

Vascular Disorders

Kawasaki disease.

General Disorders and Administration Site Conditions

Maladministration.

7 DRUG INTERACTIONS

7.1 Immunosuppressive Therapies

Immunosuppressive therapies, including irradiation, antimetabolites, alkylating agents, cytotoxic drugs, and corticosteroids (used in greater than physiologic doses), may reduce the immune response to ROTARIX. [See Warnings and Precautions (5.3).]

8 USE IN SPECIFIC POPULATIONS

8.4 Pediatric Use

Safety and effectiveness of ROTARIX in infants younger than 6 weeks or older than 24 weeks of age have not been evaluated.

The effectiveness of ROTARIX in pre-term infants has not been established. Safety data are available in pre-term infants (ROTARIX = 134, placebo = 120) with a reported gestational age ≤36 weeks. These pre-term infants were followed for SAEs up to 30 to 90 days after Dose 2. SAEs were observed in 5.2% of recipients of ROTARIX as compared with 5.0% of placebo recipients. No deaths or cases of intussusception were reported in this population.

11 DESCRIPTION

ROTARIX (Rotavirus Vaccine, Live, Oral), for oral administration, is a live, attenuated rotavirus vaccine derived from the human 89-12 strain which belongs to G1P[8] type. The rotavirus vaccine strain is propagated on Vero cells.

There are two formulations of ROTARIX: a reconstituted lyophilized formulation (supplied in a vial and oral dosing applicator presentation) and a liquid formulation (supplied in an oral dosing applicator only presentation).

Formulation for the Vial and Oral Dosing Applicator Presentation

After reconstitution of the lyophilized vaccine component, each 1 mL dose of the ROTARIX formulation for the vial and oral dosing applicator presentation contains at least 10^6.0 median Cell Culture Infective Dose (CCID50) of live, attenuated rotavirus.

The lyophilized vaccine component of this ROTARIX formulation contains amino acids, dextran, Dulbecco’s Modified Eagle Medium (DMEM), sorbitol, and sucrose. DMEM contains the following ingredients: sodium chloride, potassium chloride, magnesium sulfate, ferric (III) nitrate, sodium dihydrogen phosphate, sodium pyruvate, D-glucose, concentrated vitamin solution, L-cystine, L-tyrosine, amino acids solution, L-glutamine, calcium chloride, and sodium hydrogenocarbonate.

In the manufacturing process, porcine-derived materials are used. Porcine circovirus type 1 (PCV-1) is present in this ROTARIX formulation. PCV-1 is not known to cause disease in humans.

The liquid diluent contains calcium carbonate, sterile water, and xanthan. The diluent includes an antacid component (calcium carbonate) to protect the vaccine during passage through the stomach and prevent its inactivation due to the acidic environment of the stomach.

This ROTARIX formulation is available in single-dose vials of lyophilized vaccine, accompanied by a prefilled oral dosing applicator of liquid diluent [see How Supplied/Storage and Handling (16)]. The tip caps of the prefilled oral dosing applicators contain natural rubber latex; the vial stoppers are not made with natural rubber latex.

This ROTARIX formulation contains no preservatives.

Formulation for the Oral Dosing Applicator Only Presentation

Each 1.5 mL dose of the ROTARIX formulation for the oral dosing applicator only presentation contains at least 10^6.0 CCID50 of live, attenuated rotavirus.

This ROTARIX formulation contains disodium adipate, Dulbecco’s Modified Eagle Medium (DMEM), sucrose, and sterile water. DMEM contains the following ingredients: sodium chloride, potassium chloride, magnesium sulfate, ferric (III) nitrate, sodium dihydrogen phosphate, sodium pyruvate, D-glucose, concentrated vitamin solution, L-cystine, L-tyrosine, amino acids solution, L-glutamine, calcium chloride, and sodium hydrogenocarbonate.

This ROTARIX formulation contains an antacid component (disodium adipate) to protect the vaccine during passage through the stomach and prevent its inactivation due to the acidic environment of the stomach.

This ROTARIX formulation is available in single-dose prefilled oral dosing applicator [see How Supplied/Storage and Handling (16)]. The tip caps of the prefilled oral dosing applicators contain natural rubber latex.

This ROTARIX formulation contains no preservatives.

12 CLINICAL PHARMACOLOGY

12.1 Mechanism of Action

The exact immunologic mechanism by which ROTARIX protects against rotavirus gastroenteritis is unknown [see Clinical Studies (14.4)]. ROTARIX contains a live, attenuated human rotavirus that replicates in the small intestine and induces immunity.

12.2 Pharmacodynamics

Shedding and Transmission

A prospective, randomized, double-blind, placebo-controlled study was performed in the Dominican Republic in twins within the same household to assess whether transmission of vaccine virus occurs from a vaccinated infant to a non-vaccinated infant (Study 20; NCT00396630). One hundred pairs of healthy twins 6 to 14 weeks of age (gestational age ≥32 weeks) were randomized with one twin to receive ROTARIX (n = 100) and the other twin to receive placebo (n = 100). Twenty subjects in each arm were excluded for reasons such as having rotavirus antibody at baseline. Stool samples were collected on the day of or 1 day prior to each dose, as well as 3 times weekly for 6 consecutive weeks after each dose of ROTARIX or placebo. Transmission was defined as presence of the vaccine virus strain in any stool sample from a twin receiving placebo.

Transmitted vaccine virus was identified in 15 of 80 twins receiving placebo (18.8% [95% CI: 10.9, 29.0]). Median duration of the rotavirus shedding was 10 days in twins who received ROTARIX as compared with 4 days in twins who received placebo in whom the vaccine virus was transmitted. In the 15 twins who received placebo, no gastrointestinal symptoms related to transmitted vaccine virus were observed.

13 NONCLINICAL TOXICOLOGY

13.1 Carcinogenesis, Mutagenesis, Impairment of Fertility

ROTARIX has not been evaluated for carcinogenic or mutagenic potential, or for impairment of fertility.

14 CLINICAL STUDIES

There are two formulations of ROTARIX: a reconstituted lyophilized formulation (supplied in a vial and oral dosing applicator presentation) and a liquid formulation (supplied in an oral dosing applicator only presentation) [see Description (11)]. Efficacy was evaluated using the reconstituted lyophilized formulation [see Clinical Studies (14.1, 14.2, 14.3)]. These data are relevant to the liquid formulation because both formulations contain the same live, attenuated rotavirus strain and are manufactured using a similar process.

14.1 Efficacy Studies

The data demonstrating the efficacy of ROTARIX in preventing rotavirus gastroenteritis come from 24,163 infants randomized in two placebo-controlled studies conducted in 17 countries in Europe and Latin America (Studies 5 and 8). In these studies, oral polio vaccine (OPV) was not coadministered; however, other routine childhood vaccines could be concomitantly administered. Breastfeeding was permitted in both studies.

A randomized, double-blind, placebo-controlled study was conducted in 6 European countries (Study 5). A total of 3,994 infants were enrolled to receive ROTARIX (n = 2,646) or placebo (n = 1,348). Vaccine or placebo was given to healthy infants as a 2-dose series with the first dose administered orally from 6 through 14 weeks of age followed by one additional dose administered at least 4 weeks after the first dose. The 2-dose series was completed by 24 weeks of age. For both vaccination groups, 98.3% of infants were White and 53% were male.

The clinical case definition of rotavirus gastroenteritis was an episode of diarrhea (passage of 3 or more loose or watery stools within a day), with or without vomiting, where rotavirus was identified in a stool sample. Severity of gastroenteritis was determined by a clinical scoring system, the Vesikari scale, assessing the duration and intensity of diarrhea and vomiting, the intensity of fever, use of rehydration therapy, or hospitalization for each episode. Scores range from 0 to 20, where higher scores indicate greater severity. An episode of gastroenteritis with a score of 11 or greater was considered severe.^6

The primary efficacy endpoint was prevention of any grade of severity of rotavirus gastroenteritis caused by naturally occurring rotavirus from 2 weeks after the second dose through one rotavirus season (according to protocol, ATP). Other efficacy evaluations included prevention of severe rotavirus gastroenteritis, as defined by the Vesikari scale, and reductions in hospitalizations due to rotavirus gastroenteritis and all-cause gastroenteritis regardless of presumed etiology. Analyses were also done to evaluate the efficacy of ROTARIX against rotavirus gastroenteritis among infants who received at least one vaccination (total vaccinated cohort, TVC).

Efficacy of ROTARIX against any grade of severity of rotavirus gastroenteritis through one rotavirus season was 87.1% (95% CI: 79.6, 92.1); TVC efficacy was 87.3% (95% CI: 80.3, 92.0). Efficacy against severe rotavirus gastroenteritis through one rotavirus season was 95.8% (95% CI: 89.6, 98.7); TVC efficacy was 96.0% (95% CI: 90.2, 98.8) (Table 5). The protective effect of ROTARIX against any grade of severity of rotavirus gastroenteritis observed immediately following Dose 1 administration and prior to Dose 2 was 89.8% (95% CI: 8.9, 99.8).

Efficacy of ROTARIX in reducing hospitalizations for rotavirus gastroenteritis through one rotavirus season was 100% (95% CI: 81.8, 100); TVC efficacy was 100% (95% CI: 81.7, 100) (Table 5). ROTARIX reduced hospitalizations for all-cause gastroenteritis regardless of presumed etiology by 74.7% (95% CI: 45.5, 88.9).

Table 5. Efficacy Evaluation of ROTARIX through One Rotavirus Season
Infants in Cohort | According to Protocola |  | Total Vaccinated Cohortb
Infants in Cohort | ROTARIX | Placebo | ROTARIX | Placebo
Infants in Cohort | n = 2,572 | n = 1,302 | n = 2,646 | n = 1,348
Gastroenteritis cases
Any severity | 24 | 94 | 26 | 104
Severec | 5 | 60 | 5 | 64
Efficacy estimate against RV GE
Any severity | 87.1%d |  | 87.3%d
(95% CI) | (79.6, 92.1) |  | (80.3, 92.0)
Severec | 95.8%d |  | 96.0%d
(95% CI) | (89.6, 98.7) |  | (90.2, 98.8)
Cases of hospitalization due to RV GE | 0 | 12 | 0 | 12
Efficacy in reducing hospitalizations due to RV GE | 100%d |  | 100%d
(95% CI) | (81.8, 100) |  | (81.7, 100)
RV GE = Rotavirus gastroenteritis; CI = Confidence Interval.
a ATP analysis includes all infants in the efficacy cohort who received two doses of vaccine according to randomization.
b TVC analysis includes all infants in the efficacy cohort who received at least one dose of vaccine or placebo.
c Severe gastroenteritis defined as ≥11 on the Vesikari scale.
d Statistically significant versus placebo (P <0.001).

A randomized, double-blind, placebo-controlled study was conducted in 11 countries in Latin America and Finland (Study 8). A total of 63,225 infants received ROTARIX (n = 31,673) or placebo (n = 31,552). An efficacy subset of these infants consisting of 20,169 infants from Latin America received ROTARIX (n = 10,159) or placebo (n = 10,010). Vaccine or placebo was given to healthy infants as a 2-dose series with the first dose administered orally from 6 through 13 weeks of age followed by one additional dose administered at least 4 weeks after the first dose. The 2−dose series was completed by 24 weeks of age. For both vaccination groups, the racial distribution of the efficacy subset was as follows: Hispanic 85.8%, White 7.9%, Black 1.1%, and other 5.2%; 51% were male.

The clinical case definition of severe rotavirus gastroenteritis was an episode of diarrhea (passage of 3 or more loose or watery stools within a day), with or without vomiting, where rotavirus was identified in a stool sample, requiring hospitalization and/or rehydration therapy equivalent to World Health Organization (WHO) plan B (oral rehydration therapy) or plan C (intravenous rehydration therapy) in a medical facility.

The primary efficacy endpoint was prevention of severe rotavirus gastroenteritis caused by naturally occurring rotavirus from 2 weeks after the second dose through one year (ATP). Analyses were done to evaluate the efficacy of ROTARIX against severe rotavirus gastroenteritis among infants who received at least one vaccination (TVC). Reduction in hospitalizations due to rotavirus gastroenteritis was also evaluated (ATP).

Efficacy of ROTARIX against severe rotavirus gastroenteritis through one year was 84.7% (95% CI: 71.7, 92.4); TVC efficacy was 81.1% (95% CI: 68.5, 89.3) (Table 6).

Efficacy of ROTARIX in reducing hospitalizations for rotavirus gastroenteritis through one year was 85.0% (95% CI: 69.6, 93.5); TVC efficacy was 80.8% (95% CI: 65.7, 90.0) (Table 6).

Table 6. Efficacy Evaluation of ROTARIX through One Year
Infants in Cohort | According to Protocola |  | Total Vaccinated Cohortb
Infants in Cohort | ROTARIX | Placebo | ROTARIX | Placebo
Infants in Cohort | n = 9,009 | n = 8,858 | n = 10,159 | n = 10,010
Gastroenteritis cases
Severe | 12 | 77 | 18 | 94
Efficacy estimate against RV GE
Severe | 84.7%c |  | 81.1%c
(95% CI) | (71.7, 92.4) |  | (68.5, 89.3)
Cases of hospitalization due to RV GE | 9 | 59 | 14 | 72
Efficacy in reducing hospitalizations due to RV GE | 85.0%c |  | 80.8%c
(95% CI) | (69.6, 93.5) |  | (65.7, 90.0)
RV GE = Rotavirus gastroenteritis; CI = Confidence Interval.
a ATP analysis includes all infants in the efficacy cohort who received two doses of vaccine according to randomization.
b TVC analysis includes all infants in the efficacy cohort who received at least one dose of vaccine or placebo.
c Statistically significant versus placebo (P <0.001).

14.2 Efficacy through Two Rotavirus Seasons

The efficacy of ROTARIX persisting through two rotavirus seasons was evaluated in two studies.

In the European study (Study 5), the efficacy of ROTARIX against any grade of severity of rotavirus gastroenteritis through two rotavirus seasons was 78.9% (95% CI: 72.7, 83.8). Efficacy in preventing any grade of severity of rotavirus gastroenteritis cases occurring only during the second season post-vaccination was 71.9% (95% CI: 61.2, 79.8). The efficacy of ROTARIX against severe rotavirus gastroenteritis through two rotavirus seasons was 90.4% (95% CI: 85.1, 94.1). Efficacy in preventing severe rotavirus gastroenteritis cases occurring only during the second season post-vaccination was 85.6% (95% CI: 75.8, 91.9).

The efficacy of ROTARIX in reducing hospitalizations for rotavirus gastroenteritis through two rotavirus seasons was 96.0% (95% CI: 83.8, 99.5).

In the Latin American study (Study 8), the efficacy of ROTARIX against severe rotavirus gastroenteritis through two years was 80.5% (95% CI: 71.3, 87.1). Efficacy in preventing severe rotavirus gastroenteritis cases occurring only during the second year post-vaccination was 79.0% (95% CI: 66.4, 87.4). The efficacy of ROTARIX in reducing hospitalizations for rotavirus gastroenteritis through two years was 83.0% (95% CI: 73.1, 89.7).

The efficacy of ROTARIX beyond the second season post-vaccination was not evaluated.

14.3 Efficacy against Specific Rotavirus Types

The type-specific efficacy against any grade of severity and severe rotavirus gastroenteritis caused by G1P[8], G3P[8], G4P[8], G9P[8], and combined non-G1 (G2, G3, G4, G9) types was statistically significant through one year. Additionally, type-specific efficacy against any grade of severity and severe rotavirus gastroenteritis caused by G1P[8], G2P[4], G3P[8], G4P[8], G9P[8], and combined non-G1 (G2, G3, G4, G9) types was statistically significant through two years (Table 7).

Table 7. Type-Specific Efficacy of ROTARIX against Any Grade of Severity and Severe Rotavirus Gastroenteritis (According to Protocol)
Type Identifieda | Through One Rotavirus Season |  |  | Through Two Rotavirus Seasons
Type Identifieda | Number of Cases |  |  | Number of Cases
Type Identifieda | ROTARIX | Placebo | % Efficacy | ROTARIX | Placebo | % Efficacy
Type Identifieda | n = 2,572 | n = 1,302 | (95% CI) | n = 2,572 | n = 1,302 | (95% CI)
Any Grade of Severity
G1P[8] | 4 | 46 | 95.6%b; (87.9, 98.8) | 18 | 89c,d | 89.8%b; (82.9, 94.2)
G2P[4] | 3 | 4c | NS | 14 | 17c | 58.3%b; (10.1, 81.0)
G3P[8] | 1 | 5 | 89.9%b; (9.5, 99.8) | 3 | 10 | 84.8%b; (41.0, 97.3)
G4P[8] | 3 | 13 | 88.3%b; (57.5, 97.9) | 6 | 18 | 83.1%b; (55.6, 94.5)
G9P[8] | 13 | 27 | 75.6%b; (51.1, 88.5) | 38 | 71d | 72.9%b; (59.3, 82.2)
Combined non-G1 (G2, G3, G4, G9, G12) typese | 20 | 49 | 79.3%b; (64.6, 88.4) | 62 | 116 | 72.9%b; (62.9, 80.5)
Severe
G1P[8] | 2 | 28 | 96.4%b; (85.7, 99.6) | 4 | 57 | 96.4%b; (90.4, 99.1)
G2P[4] | 1 | 2c | NS | 2 | 7c | 85.5%b; (24.0, 98.5)
G3P[8] | 0 | 5 | 100%b; (44.8, 100) | 1 | 8 | 93.7%b; (52.8, 99.9)
G4P[8] | 0 | 7 | 100%b; (64.9, 100) | 1 | 11 | 95.4%b; (68.3, 99.9)
G9P[8] | 2 | 19 | 94.7%b; (77.9, 99.4) | 13 | 44d | 85.0%b; (71.7, 92.6)
Combined non-G1 (G2, G3, G4, G9, G12) typese | 3 | 33 | 95.4%b; (85.3, 99.1) | 17 | 70 | 87.7%b; (78.9, 93.2)
CI = Confidence Interval; NS = Not significant.
a Statistical analyses done by G type; if more than one rotavirus type was detected from a rotavirus gastroenteritis episode, the episode was counted in each of the detected rotavirus type categories.
b Statistically significant versus placebo (P <0.05).
c The P genotype was not typeable for one episode.
d P[8] genotype was not detected in one episode.
e Two cases of G12P[8] were isolated in the second season (one in each group).

14.4 Immunogenicity

A relationship between antibody responses to rotavirus vaccination and protection against rotavirus gastroenteritis has not been established. Seroconversion was defined as the appearance of anti-rotavirus IgA antibodies (concentration ≥20 U/mL) post-vaccination in the serum of infants previously negative for rotavirus.

In 2 safety and efficacy studies (Studies 5 and 8), one to two months after a 2-dose series, 86.5% of 787 recipients of ROTARIX reconstituted lyophilized formulation seroconverted compared with 6.7% of 420 placebo recipients, and 76.8% of 393 recipients of ROTARIX reconstituted lyophilized formulation seroconverted compared with 9.7% of 341 placebo recipients, respectively.

Immunogenicity of a 2-dose series of ROTARIX liquid formulation was evaluated in Study 9. This study compared seroconversion rates and Geometric Mean Concentrations (GMCs) following administration of the ROTARIX liquid formulation (n = 984) or the ROTARIX reconstituted lyophilized formulation (n = 329). The primary analyses demonstrated non-inferiority of IgA seroconversion rates and GMCs at 1 to 2 months post-vaccination for the ROTARIX liquid formulation group compared to the ROTARIX reconstituted lyophilized formulation group (Lower Limit of the 95% CI for the difference in seroconversion rates ≥-10%; Lower Limit of the 95% CI for the GMC ratio ≥0.67).

In Study 10, 3 months after a 2-dose series, the percentage of subjects with anti-rotavirus IgA antibodies (concentration ≥20 U/mL) was comparable after administration of the ROTARIX liquid formulation (76.3% of 417) and the ROTARIX reconstituted lyophilized formulation (78.9% of 426).

14.5 Concomitant Vaccine Administration

In clinical trials, ROTARIX was administered concomitantly with U.S.-licensed and non–U.S.-licensed vaccines. In a U.S. concomitant vaccine administration study (Study 18) using ROTARIX (reconstituted lyophilized formulation) in 484 infants, there was no evidence of interference in the immune responses to any of the antigens when PEDIARIX [Diphtheria and Tetanus Toxoids and Acellular Pertussis Adsorbed, Hepatitis B (Recombinant) and Inactivated Poliovirus Vaccine], a U.S.−licensed 7−valent pneumococcal conjugate vaccine (Wyeth Pharmaceuticals Inc.), and a U.S.−licensed Haemophilus b conjugate vaccine (Sanofi Pasteur SA) were concomitantly administered with ROTARIX as compared with separate administration of ROTARIX.

In a concomitant vaccine administration study (Study 10) in 1,272 infants, non-inferiority was demonstrated regarding the immune response to each of the antigens in PEDIARIX, HIBERIX [Haemophilus b Conjugate Vaccine (Tetanus Toxoid Conjugate)], and a U.S.‑licensed, 13‑valent pneumococcal conjugate vaccine (Pfizer Inc.) when concomitantly administered with the ROTARIX liquid formulation as compared to when concomitantly administered with the ROTARIX reconstituted lyophilized formulation.

15 REFERENCES

1. Murphy TV, Gargiullo PM, Massoudi MS, et al. Intussusception among infants given an oral rotavirus vaccine. N Engl J Med. 2001;344:564–572.
2. Carlin JB, Macartney KK, Lee KJ, et al. Intussusception Risk and Disease Prevention Associated with Rotavirus Vaccines in Australia’s National Immunization Program. CID. 2013;57(10):1427-1434.
3. Patel MM, López-Collada VR, Bulhões MM, et al. Intussusception Risk and Health Benefits of Rotavirus Vaccination in Mexico and Brazil. N Engl J Med. 2011;364:2283-2292.
4. Farrington CP, Whitaker HJ, Hocine MN, et al. Case series analysis for censored, perturbed, or curtailed post-event exposures. Biostatistics. 2009;10(1):3–16.
5. Tate JE, Simonsen L, Viboud C, et al. Trends in intussusception hospitalizations among US infants, 1993–2004: implications for monitoring the safety of the new rotavirus vaccination program. Pediatrics. 2008;121:e1125-e1132.
6. Ruuska T, Vesikari T. Rotavirus disease in Finnish children: use of numerical scores for severity of diarrheal episodes. Scand J Infect Dis. 1990;22:259-267.

16 HOW SUPPLIED/STORAGE AND HANDLING

16.1 ROTARIX Vial and Oral Dosing Applicator Presentation

The ROTARIX vial and oral dosing applicator presentation is supplied as single-dose vials of lyophilized vaccine component, accompanied by a prefilled oral dosing applicator of liquid diluent (1 mL) with a plunger stopper, and a transfer adapter for reconstitution.

Supplied as an outer package of 10 doses (NDC 58160-854-52) containing:

- Inner package of 10 vials of lyophilized vaccine component (NDC 58160-851-10)
  - Single vial of lyophilized vaccine component (NDC 58160-851-01)
- Oral dosing applicator of diluent (NDC 58160-853-02) (10 applicators)

Storage before Reconstitution

- Lyophilized vaccine component in vials: Store refrigerated at 2° to 8°C (36° to 46°F). Protect vials from light.
- Diluent in oral dosing applicators: Store refrigerated at 2° to 8°C (36° to 46°F) or at a controlled room temperature up to 25°C (77°F). Do not freeze. Discard if the diluent has been frozen.

Storage after Reconstitution

ROTARIX (vial and oral dosing applicator presentation) should be administered within 24 hours of reconstitution. After reconstitution, store refrigerated at 2° to 8°C (36° to 46°F) or at a controlled room temperature up to 25°C (77°F). Discard the reconstituted vaccine in biological waste container if not used within 24 hours. Do not freeze. Discard if the reconstituted vaccine has been frozen.

16.2 ROTARIX Oral Dosing Applicator Only Presentation

ROTARIX oral dosing applicator only presentation is supplied as a single, 1.5-mL dose in a prefilled oral dosing applicator with a plunger stopper (NDC 58160-740-02) in a carton of 10 (NDC 58160-740-21).

Storage

Store refrigerated at 2° to 8℃ (36° to 46°F). Do not freeze. Discard if the vaccine has been frozen. Keep in original package to protect from light.

17 PATIENT COUNSELING INFORMATION

See FDA-approved patient labeling (Patient Information). Patient labeling is provided as a tear-off leaflet at the end of this full prescribing information.

Provide the following information to the parent or guardian:

- Inform of the potential benefits and risks of immunization with ROTARIX, and of the importance of completing the immunization series.
- Inform about the potential for adverse reactions that have been temporally associated with administration of ROTARIX or other vaccines containing similar components.
- Instruct to immediately report any signs and/or symptoms of intussusception to their healthcare provider.
- Give the Vaccine Information Statements, which are required by the National Childhood Vaccine Injury Act of 1986 to be given prior to immunization. These materials are available free of charge at the Centers for Disease Control and Prevention (CDC) website (www.cdc.gov/vaccines).

ROTARIX, PEDIARIX, and HIBERIX are owned by or licensed to the GSK group of companies. The other brands listed are trademarks owned by or licensed to their respective owners and are not owned by or licensed to the GSK group of companies. The makers of these brands are not affiliated with and do not endorse the GSK group of companies or its products.

Manufactured by GlaxoSmithKline Biologicals
Rixensart, Belgium, U.S. License 1617
Distributed by GlaxoSmithKline
Durham, NC 27701
©2024 GSK group of companies or its licensor.
RTX:20PI

PATIENT INFORMATION

ROTARIX (ROW-tah-rix)

Rotavirus Vaccine, Live, Oral

What is ROTARIX?

ROTARIX is a vaccine that protects your baby from a kind of virus (called a rotavirus) that can cause bad diarrhea and vomiting. Rotavirus can cause diarrhea and vomiting that is so bad that your baby can lose too much body fluid and need to go to the hospital.

Rotavirus vaccine is a liquid that is given to your baby by mouth. It is not an injection.

Who should not take ROTARIX?

Your baby should not get ROTARIX if:

- he or she has had an allergic reaction after getting a dose of ROTARIX.
- he or she is allergic to any of the ingredients of this vaccine. A list of ingredients can be found at the end of this leaflet.
- a doctor has told you that your baby’s digestive system has a defect (is not normal).
- he or she has a history of a serious problem called intussusception that happens when a part of the intestine gets blocked or twisted.
- he or she has Severe Combined Immunodeficiency Disease (SCID), a severe problem with his/her immune system.

Tell your doctor if your baby:

- is allergic to latex.
- has problems with his/her immune system.
- has cancer.
- will be in close contact with someone who has problems with his/her immune system or is getting treated for cancer, as the spread of vaccine virus to non-vaccinated contacts could occur. Hand washing is recommended after diaper changes to help prevent the spread of vaccine virus.

If your baby has been having diarrhea and vomiting, your doctor may want to wait before giving your baby a dose of ROTARIX.

How is ROTARIX given?

ROTARIX is a liquid that is dropped into your baby’s mouth and swallowed.

Your baby will get the first dose at around 6 weeks old.

The second dose will be at least 4 weeks after the first dose (before 6 months old).

Be sure to plan the time for your baby’s second dose with the doctor because it is important that your baby gets both doses of ROTARIX before your baby is 6 months old.

The doctor may decide to give your baby other vaccines at the same time as ROTARIX.

Your baby can be fed normally after getting ROTARIX.

What are possible side effects of ROTARIX?

The most common side effects of ROTARIX are:

- crying
- fussiness
- cough
- runny nose
- fever
- loss of appetite
- vomiting.

Call your doctor right away or go to the emergency department if your baby has any of these problems after getting ROTARIX, even if it has been several weeks since the last vaccine dose because these may be signs of a serious problem called intussusception:

- bad vomiting
- bad diarrhea
- bloody bowel movement
- high fever
- severe stomach pain (if your baby brings his/her knees to his/her chest while crying or screaming).

Studies showed an increased risk of intussusception after the first and second dose of vaccine, especially in the first 7 days.

Since FDA approval, reports of infants with intussusception have been received by Vaccine Adverse Event Reporting System (VAERS). Intussusception occurred days and sometimes weeks after vaccination. Some infants needed hospitalization, surgery on their intestines, or a special enema to treat this problem. Death due to intussusception has occurred.

Other reported side effects include: Kawasaki disease (a serious condition that can affect the heart; symptoms may include fever, rash, red eyes, red mouth, swollen glands, swollen hands and feet, and, if not treated, death can occur).

Talk to your baby’s doctor if your baby has any problems that concern you.

What are the ingredients in ROTARIX?

There are two formulations of Rotarix, one that requires your vaccination provider to mix a freeze-dried component with a liquid component and one that is provided as a liquid that does not require mixing. Your provider can tell you the formulation your baby will receive.

Formulation that requires mixing

This formulation of ROTARIX contains weakened human rotavirus.

This formulation of ROTARIX also contains calcium carbonate, dextran, sorbitol, sucrose, amino acids, xanthan, Dulbecco’s Modified Eagle Medium (DMEM), and sterile water. The ingredients of DMEM are as follows: sodium chloride, potassium chloride, magnesium sulphate, ferric (III) nitrate, sodium dihydrogen phosphate, sodium pyruvate, D-glucose, concentrated vitamin solution, L-cystine, L-tyrosine, amino acids solution, L-glutamine, calcium chloride, and sodium hydrogenocarbonate.

Porcine circovirus type 1 (PCV-1), a virus found in pigs, is present in this formulation of ROTARIX. PCV-1 is not known to cause disease in humans.

This formulation of ROTARIX contains no preservatives.

The tip cap of the dropper used to give your baby ROTARIX contains latex.

Formulation that does not require mixing

This formulation of ROTARIX contains weakened human rotavirus.

This formulation of ROTARIX also contains disodium adipate, sucrose, Dulbecco’s Modified Eagle Medium (DMEM), and sterile water. The ingredients of DMEM are as follows: sodium chloride, potassium chloride, magnesium sulphate, ferric (III) nitrate, sodium dihydrogen phosphate, sodium pyruvate, D-glucose, concentrated vitamin solution, L-cystine, L-tyrosine, amino acids solution, L-glutamine, calcium chloride, and sodium hydrogenocarbonate.

This formulation of ROTARIX contains no preservatives.

The tip cap of the dropper used to give your baby ROTARIX contains latex.

Manufactured by GlaxoSmithKline Biologicals

Rixensart, Belgium, U.S. License 1617

Distributed by GlaxoSmithKline

Durham, NC 27701

Trademarks are owned by or licensed to the GSK group of companies.

©2022 GSK group of companies or its licensor.

RTX:15PIL

This Patient Information has been approved by the U.S. Food and Drug Administration.

Revised: 11/2022

PACKAGE LABEL

PRINCIPAL DISPLAY PANEL

NDC 58160-740-21

ROTARIX

Rotavirus Vaccine, Live, Oral

FOR ORAL USE ONLY.

Rx only

For ORAL USE ONLY.

Do not inject.

Do not reconstitute.

For Use from 6 to 24 Weeks of Age

Contents (10 doeses of ROTARIX:

10 Single-Dose Prefilled Oral Dosing Applicators each containing one dose of 1.5 mL

Made in Belgium

©2022 GSK group of companies or its licensor.

Rev. 9/22

509532